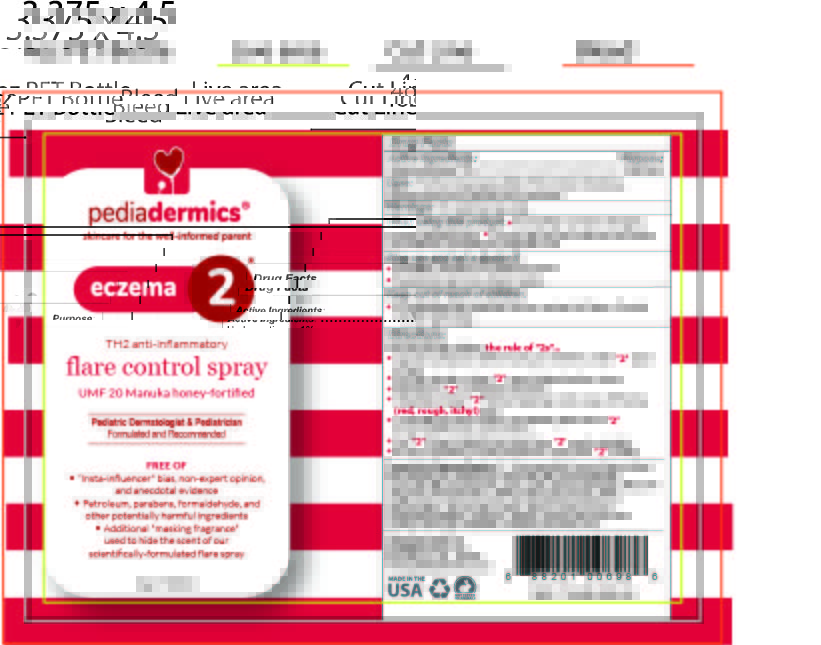 DRUG LABEL: PEDIADERMICS ECZEMA 2
NDC: 76348-585 | Form: SPRAY
Manufacturer: RENU LABORATORIES, LLC
Category: otc | Type: HUMAN OTC DRUG LABEL
Date: 20251202

ACTIVE INGREDIENTS: HYDROCORTISONE 1.12 g/112 g
INACTIVE INGREDIENTS: 1,2-HEXANEDIOL; SORBITOL SOLUTION 70%; OAT; SODIUM CITRATE; HONEY; PHYTOSPHINGOSINE; HYALURONATE SODIUM; CITRIC ACID MONOHYDRATE; MALTODEXTRIN; CHOLESTEROL; SODIUM LAUROYL LACTYLATE; PHENOXYETHANOL; ETHYLHEXYLGLYCERIN; CARBOMER HOMOPOLYMER, UNSPECIFIED TYPE; XANTHAN GUM; WATER; CERAMIDE 1; CERAMIDE NP; CERAMIDE AP; GLYCERIN

PEDIADERMICS ECZEMA 2

STATEMENT OF IDENTITY

pediadermics Eczema 2 flare control spray

Active Ingredients:

Hydrocortisone 1%

Purpose

Anti-itch

Uses:

For the temporary relief of minor skin irritations, inflammation and rashes due to eczema

Warnings For external use only

When using this product

- Avoid direct contact with eyes, mouth, genitals/anus
- Do not use for treatment of diaper rash without consulting a physician first

Stop use and ask a doctor if

- Condition worsens or irritation occurs
- Symptoms last more than 2 weeks

Keep out of reach of children

- If swallowed get medical help or contact a Poison Control Center right away

Directions

For best results follow the rule of "2s" ...

- Consult a physician before using on children under "2" years of age
- Give the bottle at least "2" good shakes before using
- Hold the botle about "2" inches from the skin
- Dispense at least "2" full pump sprays onto areas of flaring (red, rough, itchy) skin
- Cover flaring areas of skin completely plus about "2" finger-widths onto normal skin
- Use "2" times a day for no more than "2" weeks straight.
- Go to a physician if rash persists for more than "2" weeks

Dosage and Administration - NO Major Changes at all

Inactive Ingredients

1, 2 Hexanediol, Avena Sativa (Oat) Kernel Extract, Carbomer, Ceramide AP, Ceramide EOP, Ceramide NP, Cholesterol, Citric Acid, Deionized Water, Glycerin (Vegetal), Maltodextrin, UMF-20 Manuka Honey (20%), Ophiopogon Japonicus (Dwarf Lilyturf) Root Extract, Phytosphingosine, Sodium Citrate, Sodium Hyaluronate, Sodium Lauroyl Lactylate, Sorbitol, Xanthan Gum

STATEMENT OF IDENTITY

Manufactured for Pediadermics LLC

Bethlehem PA 18018

www.pediadermics.com

PACKAGE LABEL

BOTTLE ARTWORK